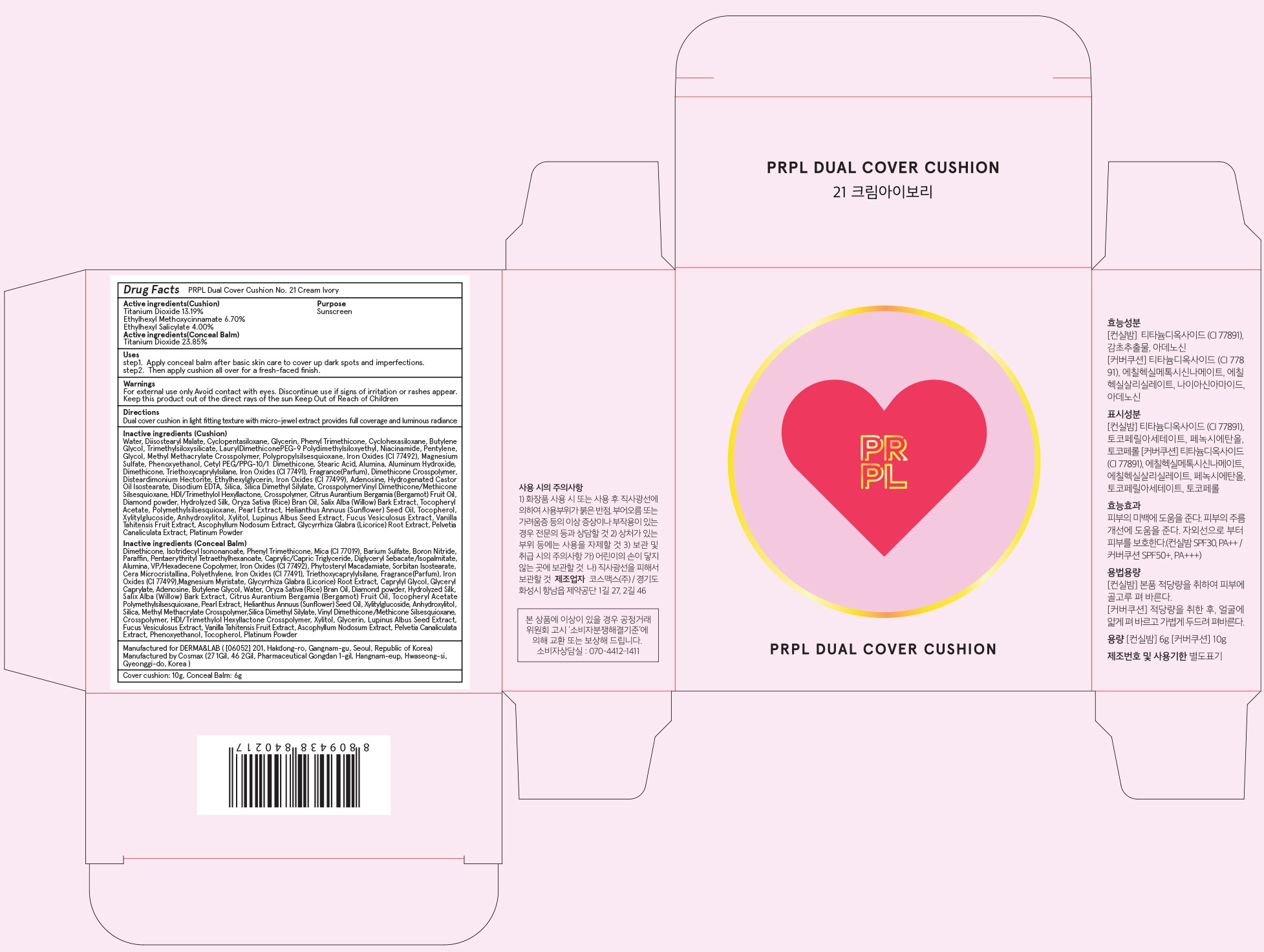 DRUG LABEL: PRPL dual cover cushion No 21 cre am ivory Conceal Balm
NDC: 71725-020 | Form: POWDER
Manufacturer: Derma&lab Co., Ltd.
Category: otc | Type: HUMAN OTC DRUG LABEL
Date: 20171019

ACTIVE INGREDIENTS: Titanium Dioxide 1.43 g/6 g
INACTIVE INGREDIENTS: Dimethicone; Isotridecyl Isononanoate

ACTIVE INGREDIENT

Active ingredients: Titanium Dioxide 23.85%

INACTIVE INGREDIENT

Inactive ingredients: Dimethicone, Isotridecyl Isononanoate, Phenyl Trimethicone, Mica (CI 77019), Barium Sulfate, Boron Nitride, Paraffin, Pentaerythrityl Tetraethylhexanoate, Caprylic/Capric Triglyceride, Diglyceryl Sebacate/Isopalmitate, Alumina, VP/Hexadecene Copolymer, Iron Oxides (CI 77492), Phytosteryl Macadamiate, Sorbitan Isostearate, Cera Microcristallina, Polyethylene, Iron Oxides (CI 77491), Triethoxycaprylylsilane, Fragrance(Parfum), Iron Oxides (CI 77499), Magnesium Myristate, Glycyrrhiza Glabra (Licorice) Root Extract, Caprylyl Glycol, Glyceryl Caprylate, Adenosine, Butylene Glycol, Water, Oryza Sativa (Rice) Bran Oil, Diamond powder, Hydrolyzed Silk, Salix Alba (Willow) Bark Extract, Citrus Aurantium Bergamia (Bergamot) Fruit Oil, Tocopheryl Acetate Polymethylsilsesquioxane, Pearl Extract, Helianthus Annuus (Sunflower) Seed Oil, Xylitylglucoside, Anhydroxylitol, Silica, Methyl Methacrylate Crosspolymer, Silica Dimethyl Silylate, Vinyl Dimethicone/Methicone Silsesquioxane, Crosspolymer, HDI/Trimethylol Hexyllactone Crosspolymer, Xylitol, Glycerin, Lupinus Albus Seed Extract, Fucus Vesiculosus Extract, Vanilla Tahitensis Fruit Extract, Ascophyllum Nodosum Extract, Pelvetia Canaliculata Extract, Phenoxyethanol, Tocopherol, Platinum Powder

PURPOSE

Purpose: Sunscreen

WARNINGS

Warnings: For external use only. Avoid contact with eyes. Discontinue use if signs of irritation or rashes appear. Keep this product out of the direct rays of the sun. Keep Out of Reach of Children.

DESCRIPTION

Uses:

step1. Apply conceal balm after basic skin care to cover up dark spots and imperfections.

step2. Then apply cushion all over for a fresh-faced finish.

Directions: Dual cover cushion in light fitting texture with micro-jewel extract provides full coverage and luminous radiance